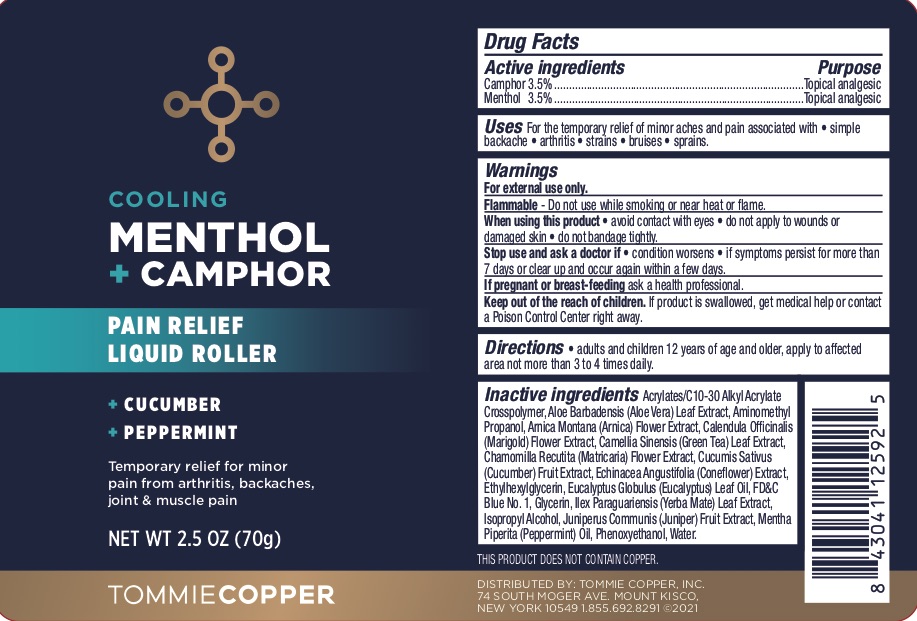 DRUG LABEL: Pain Relief Liquid Roller
NDC: 72562-167 | Form: LIQUID
Manufacturer: Tommie Copper, Inc.
Category: otc | Type: HUMAN OTC DRUG LABEL
Date: 20241215

ACTIVE INGREDIENTS: MENTHOL 3.5 g/100 g; CAMPHOR (SYNTHETIC) 3.5 g/100 g
INACTIVE INGREDIENTS: GLYCERIN; ECHINACEA, UNSPECIFIED; ETHYLHEXYLGLYCERIN; EUCALYPTUS OIL; FD&C BLUE NO. 1; CARBOMER INTERPOLYMER TYPE A (ALLYL SUCROSE CROSSLINKED); CALENDULA OFFICINALIS FLOWER; ISOPROPYL ALCOHOL; JUNIPER BERRY; ALOE VERA LEAF; AMINOMETHYLPROPANOL; ARNICA MONTANA FLOWER; CUCUMBER; ILEX PARAGUARIENSIS LEAF; PEPPERMINT OIL; PHENOXYETHANOL; WATER; GREEN TEA LEAF; CHAMOMILE

Pain Relief Liquid Roller

ACTIVE INGREDIENT

Camphor 3.5%, Menthol 3.5%

PURPOSE

Topical Analgesic

INDICATIONS AND USAGE

For the temporary relief of minor aches and pain associated with simple backaches, arthritis, strains, bruises, and sprains.

WARNINGS

For external use only. Flammable--Do not use while smoking or near heat or flame. When using this product avoid contact with eyes, do not apply to wounds or damaged skin, and do not bandage tightly. Stop use and ask a doctor if condition worsens, if symptoms persist for more than 7 days or clear up and occur again within a few days.

PREGNANCY OR BREAST FEEDING

If pregnant or breast-feeding ask a health professional.

KEEP OUT OF REACH OF CHILDREN

If swallowed, get medical help or contact a Poison Control Center right away.

DOSAGE AND ADMINISTRATION

Adults and children 12 years of age and older, apply to the affected area not more than 3 to 4 times daily.

INACTIVE INGREDIENT

Acrylates/C10-30 Alkyl Acrylate Crosspolymer, Aloe Barbadensis (Aloe Vera) Leaf Extract, Aminomethyl Propanol, Arnica Montana (Arnica) Flower Extract, Calendula Officinalis (Marigold) Flower Extract, Camellia Sinensis (Green Tea) Leaf Extract, Chamomilla Recutita (Matricaria) Flower Extract, Cucumis Sativus (Cucumber) Fruit Extract, Echinacea Angustifolia (Coneflower) Extract, Ethyhexylglycerin, Eucalyptus Globulus (Eucalyptus) Leaf Oil, FD&C Blue No 1, Glycerin, Ilex Paraguariensis (Yerba Mate) Leaf Extract, Isopropyl Alcohol, Juniperus Communis (Juniper) Fruit Extract, Mentha Piperita (Peppermint) Oil, Phenoxyethanol, Water.